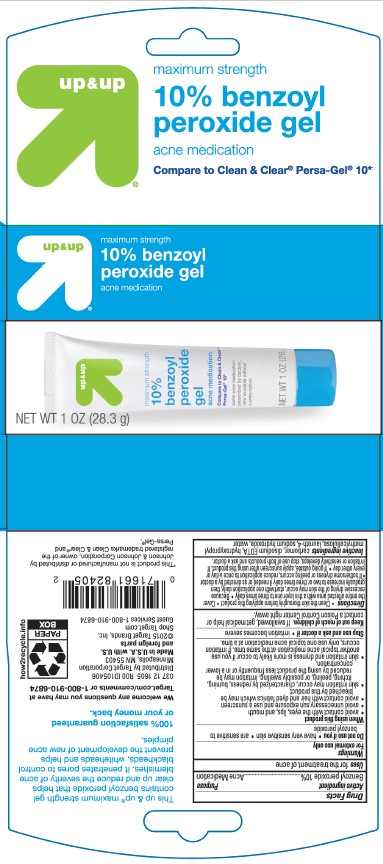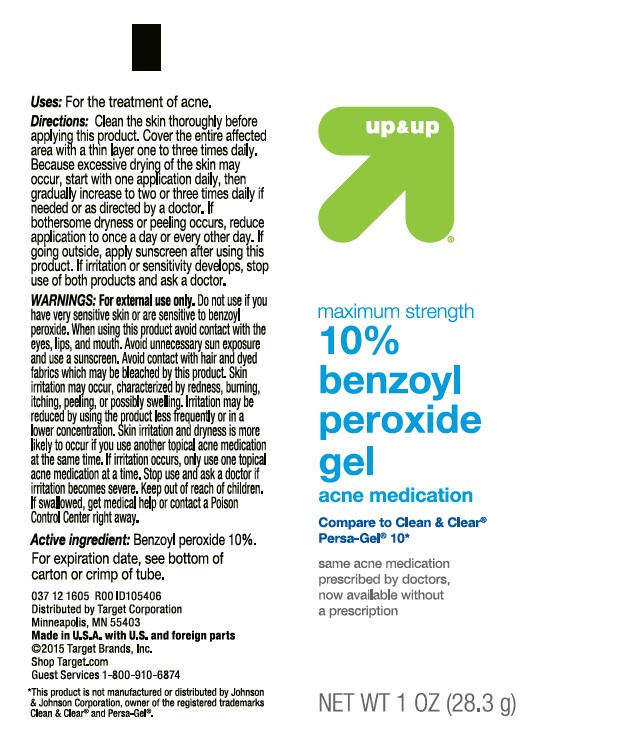 DRUG LABEL: TARGET UP AND UP ACNE MEDICATION
NDC: 11673-088 | Form: GEL
Manufacturer: TARGET CORPORATION
Category: otc | Type: HUMAN OTC DRUG LABEL
Date: 20241014

ACTIVE INGREDIENTS: BENZOYL PEROXIDE 100 mg/1 g
INACTIVE INGREDIENTS: CARBOMER INTERPOLYMER TYPE A (ALLYL SUCROSE CROSSLINKED); EDETATE DISODIUM; HYPROMELLOSE 2910 (4000 MPA.S); LAURETH-4; SODIUM HYDROXIDE; WATER

TARGET UP & UP 10% BENZOYL PEROXIDE ACNE MEDICATION

Active ingredient

Benzoyl Peroxide 10%

Purpose

Acne Medication

Uses

for the treatment of acne

Warnings

For external use only

Do not use if you

- have very sensitive skin • are sensitive to benzoyl peroxide

When using this product

- avoid contact with the eyes, lips, and mouth
- avoid unnecessary sun exposure and use a sunscreen
- avoid contact with hair and dyed fabrics which may be bleached by this product
- skin irritation may occur, characterized by redness, burning, itching, peeling, or possibly swelling. Irritation may be reduced by using the product less frequently or in a lower concentration.
- skin irritation and dryness is more likely to occur if you use another topical acne medication at the same time. If irritation occurs, only use one topical acne medication at a time.

Stop use and ask a doctor if

• irritation becomes severe

Keep out of reach of children.

If swallowed, get medical help or contact a Poison Control Center right away.

Directions

- Clean the skin thoroughly before applying this product
- Cover the entire affected area with a thin layer one to three times daily
- Becasue excessive drying of the skin may occur, start with one application daily, then gradually increase to two or three times daily if needed or as directed by a doctor
- If bothersome dryness or peeling occurs, reduce application to once a day or every other day
- If going outside, apply sunscreen after using this product. If irritation or sensitivity develops, stop use of both products and ask a doctor.

Inactive ingredients

carbomer, disodium EDTA, hydroxypropyl methylcellulose, laureth-4, sodium hydroxide, water

Label

TARGET UP & UP ACNE MEDICATION 10% BENZOYL PEROXIDE GEL

1 OZ (28.3g)

NDC 11673-088-16

TARGET UP & UP ACNE MEDICATION 10% BENZOYL PEROXIDE GEL

BLISTER PACK

NDC 11673-088-17